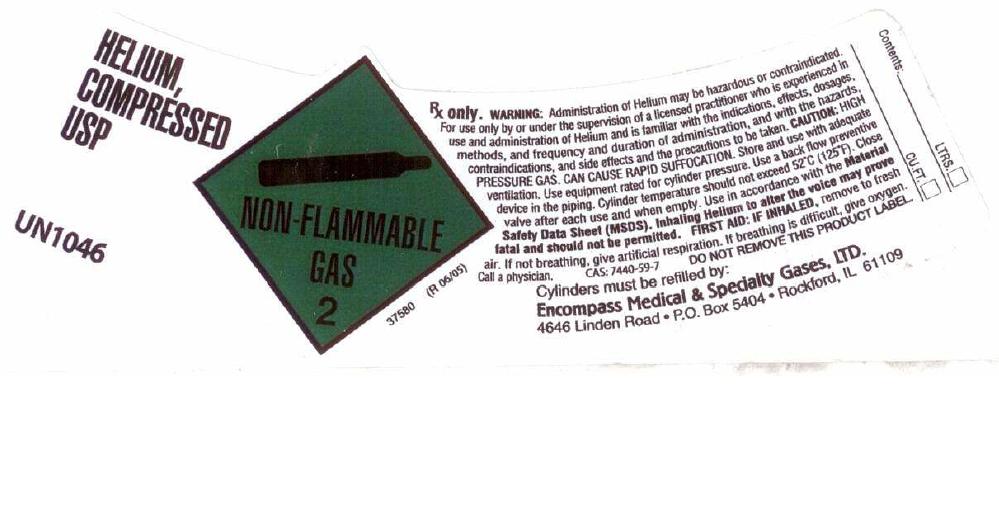 DRUG LABEL: Helium
NDC: 48883-006 | Form: GAS
Manufacturer: Encompass Medical & Specialty Gases, Ltd.
Category: prescription | Type: HUMAN PRESCRIPTION DRUG LABEL
Date: 20101220

ACTIVE INGREDIENTS: Helium 990 mL/1 L

Helium Label

PACKAGE LABEL

HELIUM COMPRESSED, USP UN1046
NON-FLAMMABLE GAS 2 37580 (R 06/05)
Rx only. WARNING: Administration of Helium may be hazardous or contraindicated. For use only by or under supervision of a licensed practitioner who is experienced in the use and administration of Helium and is familiar with the indications, effects, dosages, methods, and frequency and duration of administration, and with the hazards, contraindications, and side effects and the precautions to be taken. CAUTION: HIGH PRESSURE GAS. CAN CAUSE RAPID SUFFOCATION. Store and use with adequate ventilation. Use equipment rated for cylinder pressure. Use a back flow preventive device in the piping. Cylinder temperatures should not exceed 52C (125F). Close valve after each use and when empty. Use in accordance with the Material Safety Data Sheet (MSDS). Inhaling Helium to alter the voice may prove fatal and should not be permitted. FIRST AID: IF INHALED, remove to fresh air. If not breathing, give artificial respiration. If breathing is difficult, give oxygen. Call a physician. CAS: 7440-59-7
DO NOT REMOVE THIS PRODUCT LABEL.
Cylinders must be refilled by:
Encompass Medical and Specialty Gases, LTD. 4646 Linden Road P.O. Box 5404 Rockford, IL 61109
CONTENTS: LTRS CU. FT.